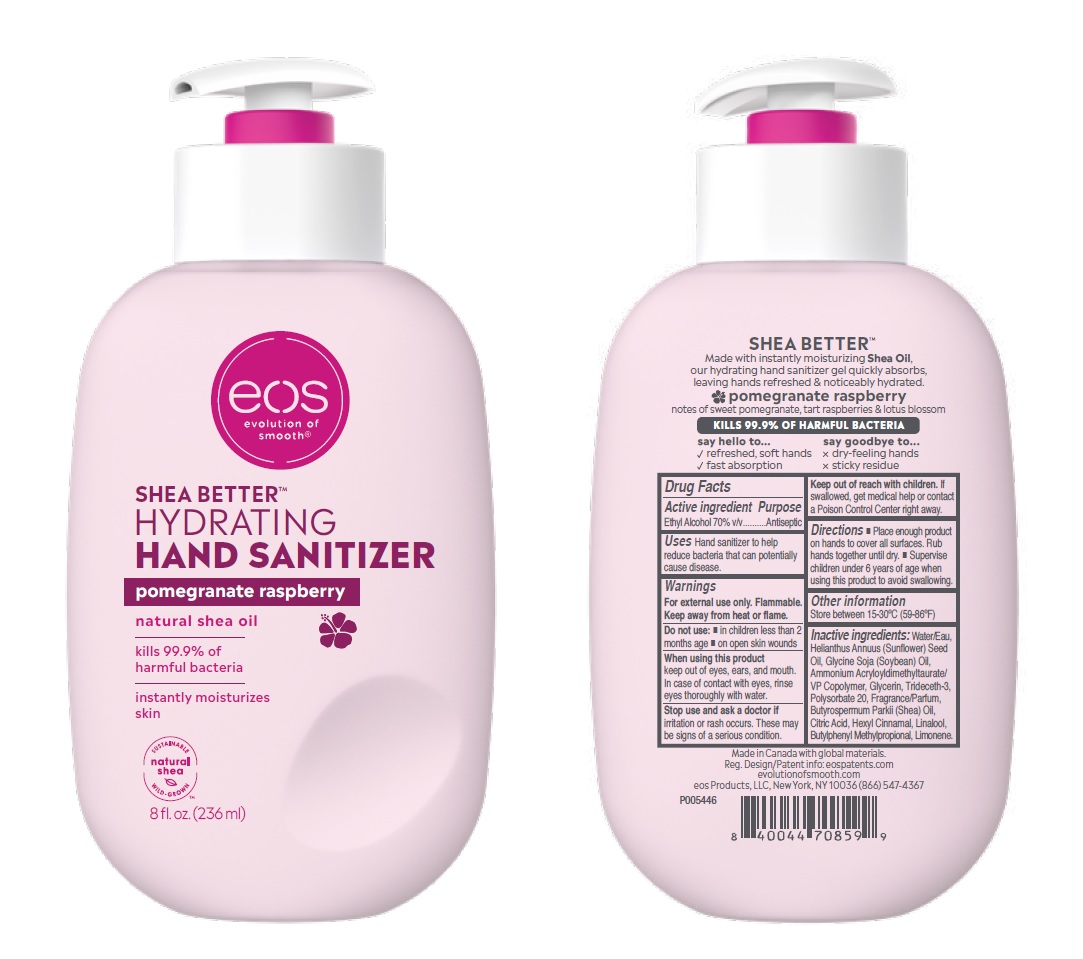 DRUG LABEL: eos SHEA BETTERTM HYDRATING HAND SANITIZER pomegranate raspberry
NDC: 70170-0020 | Form: GEL
Manufacturer: eos Products LLC
Category: otc | Type: HUMAN OTC DRUG LABEL
Date: 20241030

ACTIVE INGREDIENTS: ALCOHOL 165.2 mL/236 mL
INACTIVE INGREDIENTS: WATER; SUNFLOWER OIL; SOYBEAN OIL; AMMONIUM ACRYLOYLDIMETHYLTAURATE/VP COPOLYMER; GLYCERIN; TRIDECETH-3; POLYSORBATE 20; SHEANUT OIL; CITRIC ACID MONOHYDRATE; .ALPHA.-HEXYLCINNAMALDEHYDE; LINALOOL, (+)-; BUTYLPHENYL METHYLPROPIONAL; LIMONENE, (+)-; .BETA.-CITRONELLOL, (+/-)-; HYDROXYCITRONELLAL; ISOMETHYL-.ALPHA.-IONONE; CITRAL; BENZYL ALCOHOL; .ALPHA.-AMYLCINNAMYL ACETATE; GERANIOL; BENZYL SALICYLATE; ANISYL ALCOHOL

eos SHEA BETTERTMHYDRATING HAND SANITIZER pomegranate raspberry

Active ingredients Purpose

Ethyl Alcohol, 70% v/v Antiseptic

Uses

Hand sanitizer to help reduce bacteria that can potentially cause disease.

Warnings

For external use only. Flammable. Keep away from heat or flame.

Do not use:

- in children less than 2 months age
- on open skin wounds

WHEN USING

When using this productkeep out of eyes, ears, and mouth. In case of contact with eyes, rinse eyes thoroughly with water.

Stop use and ask a doctor ifirritation or rash occurs. These may be signs of a serious condition.

KEEP OUT OF REACH OF CHILDREN

Keep out of reach with children.If swallowed, get medical help or contact a Poison Control Center right away.

Directions

- Place enough product on hands to cover all surfaces. Rub hands together until dry.
- Supervise children under 6 years of age when using this product to avoid swallowing.

Other information

Store between 15-30ºC (59-86ºF)

Inactive ingredients:

Water/Eau, Helianthus Annuus (Sunflower) Seed Oil, Glycine Soja (Soybean) Oil, Ammonium Acryloyldimethyltaurate/VP Copolymer, Glycerin, Trideceth-3, Polysorbate 20, Fragrance/Parfum, Butyrospermum Parkii (Shea) Oil, Citric Acid, Hexyl Cinnamal, Linalool, Butylphenyl Methylpropional, Limonene.

Principal Display Panel - 8 fl. oz. (236 ml)

eos

SHEA BETTERTM

HYDRATING

HAND SANITIZER

pomegranate raspberry

natural shea oil

kills 99.9% of

harmful bacteria

instantly moisturizes

skin

8 fl. oz. (236 ml)